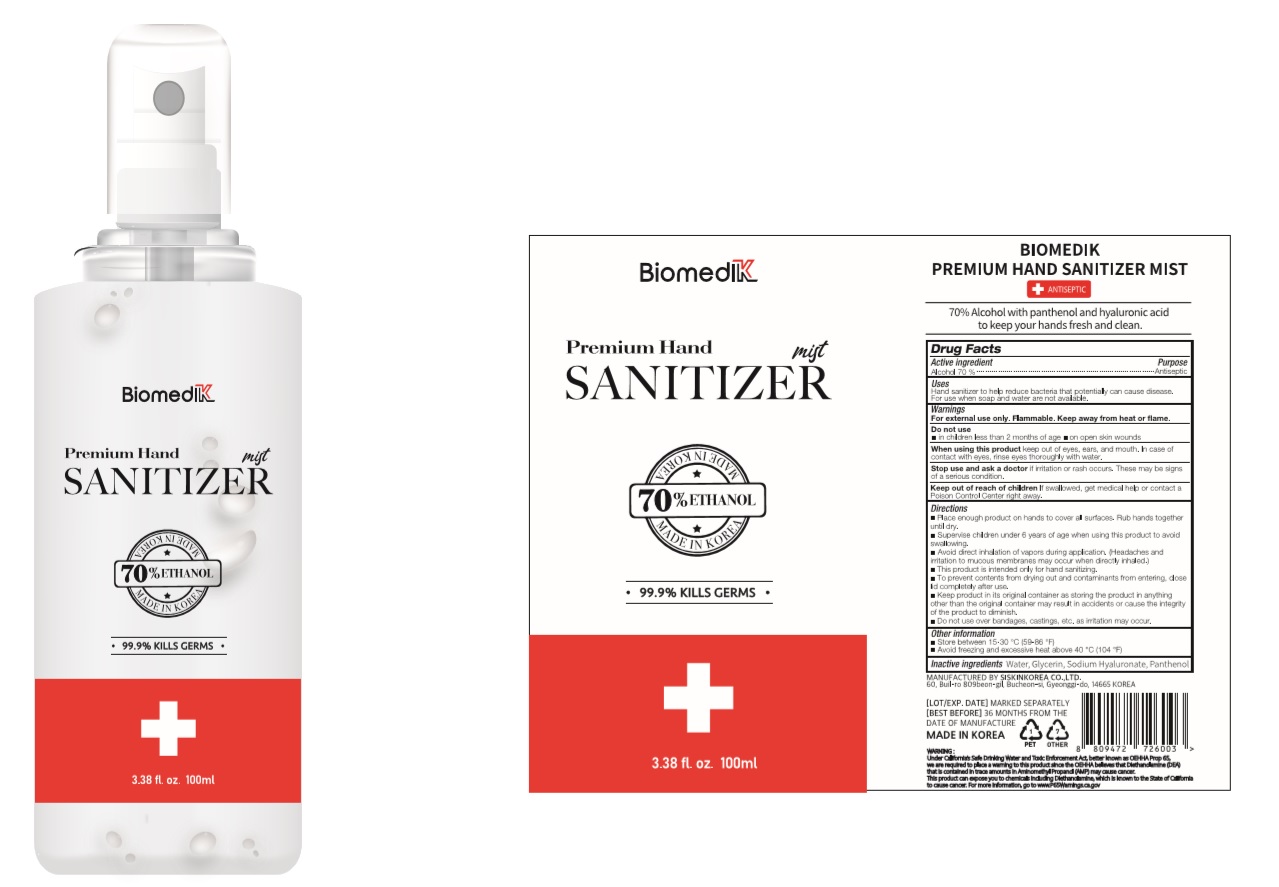 DRUG LABEL: BIOMEDIK Premium Hand Sanitizer Mist
NDC: 74514-7100 | Form: SPRAY
Manufacturer: SISKINKOREA CO.,LTD.
Category: otc | Type: HUMAN OTC DRUG LABEL
Date: 20200616

ACTIVE INGREDIENTS: ALCOHOL 70 mL/100 mL
INACTIVE INGREDIENTS: GLYCERIN; PANTHENOL; WATER; HYALURONATE SODIUM

BIOMEDIK Premium Hand Sanitizer Mist | Bottle+Spray | 74514-7100-1